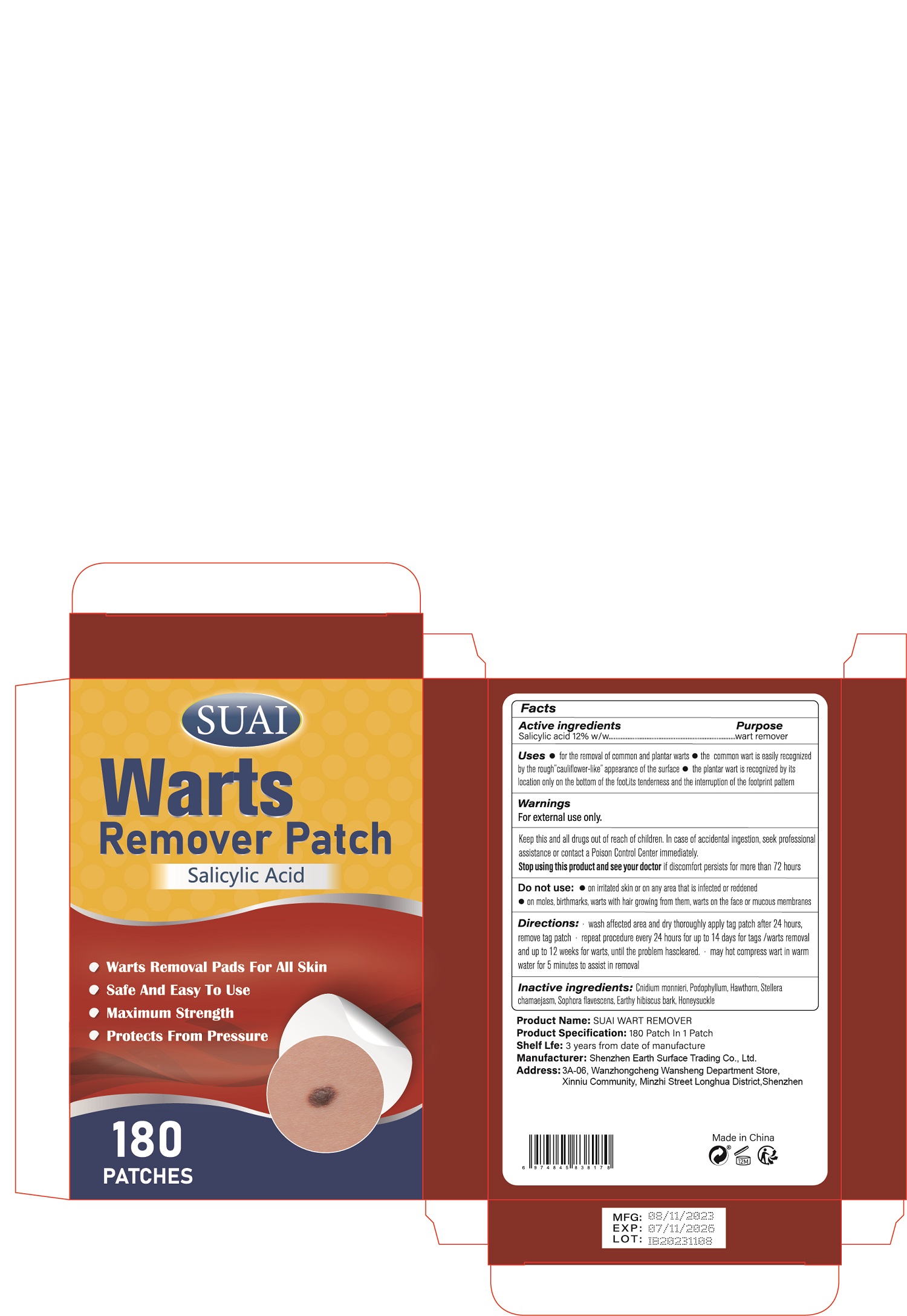 DRUG LABEL: Wart Remover Patch
NDC: 85636-003 | Form: PATCH
Manufacturer: Shenzhen Earth Surface Trading Co., Ltd.
Category: otc | Type: HUMAN OTC DRUG LABEL
Date: 20250616

ACTIVE INGREDIENTS: SALICYLIC ACID 12 g/100 1
INACTIVE INGREDIENTS: PODOPHYLLUM; HAWTHORN LEAF WITH FLOWER; LONICERA JAPONICA FLOWER; STELLERA CHAMAEJASME WHOLE; HIBISCUS SYRIACUS BARK; SOPHORA FLAVESCENS ROOT; CNIDIUM MONNIERI FRUIT OIL

ACTIVE INGREDIENT

Salicylic acid

Purpose

wart remover

Uses

Use

● for the removal of common and plantar warts

● the common wart is easily recognized by the roughcauliflower-like appearance of the surface

● the plantar wart is recognized by its location only on the bottom of the foot,its tenderness and the interruption of the footprint pattern

Warnings

For external use only.
Keep this and all drugs out of reach of children. In case of accidental ingestion, seek professional assistance or contact a Poison Control Center immediately.
Stop using this product and see your doctor if discomfort persists for more than 72 hours

When using this product :

●on irritated skin or on any area that is infected or reddened

●on moles, birthmarks, warts with hair growing from them, warts on the face or mucous membranes

Keep Out Of Reach Of Children

Directions Of Safe Use:

● wash affected area and dry thoroughly apply tag patch after 24 hours. remove tag patch

● repeat procedure every 24 hours for up to 14 days for tags /warts removal and up to 12 weeks for warts, until the problem hascleared.

● may hot compress wart in warm water for 5 minutes to assist in removal

Stop use and ask a doctor:

· if discomfort persists.·if you have diabetes
or poor blood circulation.Keep out of reach
of children. lf swallowed, get medical help
or contact a Poison Control Center right
away.

Inactive ingredients

Cnidium monnieri, Podophyllum,Hawthorn, Stellera chamaejasm, Sophora flavescens, Earthy hibiscus bark, Honeysuckle